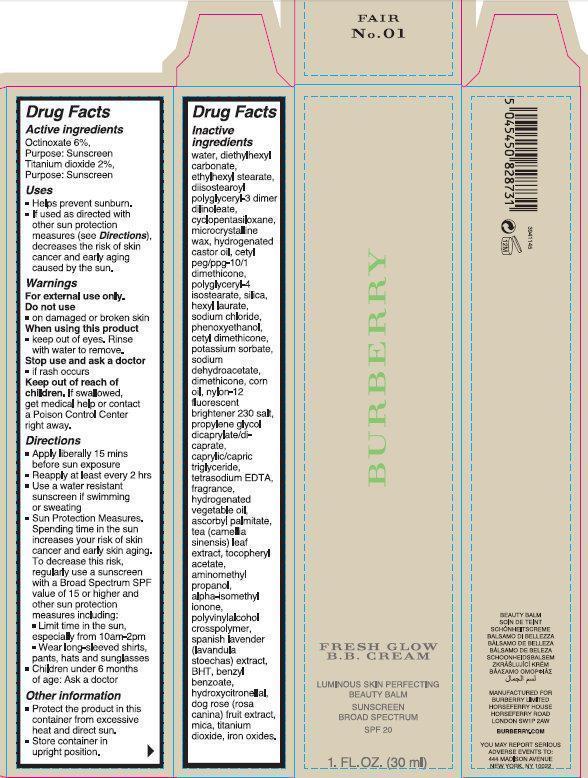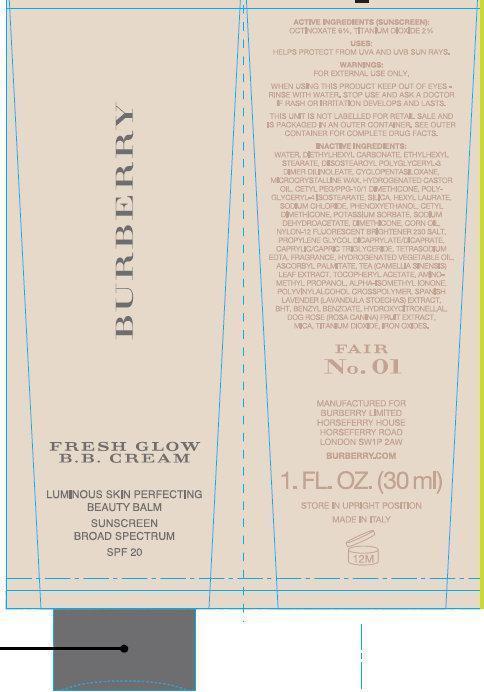 DRUG LABEL: BURBERRY FRESH GLOW B.B. LUMINOUS SKIN PERFECTING BEAUTY BALM SUNSCREEN BROAD SPECTRUM SPF 20 FAIR 01
                        
NDC: 69038-001 | Form: CREAM
Manufacturer: Burberry Limited
Category: otc | Type: HUMAN OTC DRUG LABEL
Date: 20141113

ACTIVE INGREDIENTS: OCTINOXATE 60 mg/1 mL; TITANIUM DIOXIDE 20 mg/1 mL
INACTIVE INGREDIENTS: WATER; DIETHYLHEXYL CARBONATE; ETHYLHEXYL STEARATE; DIISOSTEAROYL POLYGLYCERYL-3 DIMER DILINOLEATE; CYCLOMETHICONE 5; MICROCRYSTALLINE WAX; HYDROGENATED CASTOR OIL; POLYGLYCERYL-4 ISOSTEARATE; SILICON DIOXIDE; HEXYL LAURATE; SODIUM CHLORIDE; PHENOXYETHANOL; POTASSIUM SORBATE; SODIUM DEHYDROACETATE; DIMETHICONE; CORN OIL; PROPYLENE GLYCOL DICAPRYLATE/DICAPRATE; MEDIUM-CHAIN TRIGLYCERIDES; EDETATE SODIUM; ASCORBYL PALMITATE; GREEN TEA LEAF; .ALPHA.-TOCOPHEROL ACETATE; AMINOMETHYLPROPANOL; ISOMETHYL-.ALPHA.-IONONE; LAVANDULA STOECHAS WHOLE; BUTYLATED HYDROXYTOLUENE; BENZYL BENZOATE; HYDROXYCITRONELLAL; ROSA CANINA FRUIT; MICA; FERRIC OXIDE RED

BURBERRY FRESH GLOW B.B. CREAM LUMINOUS SKIN PERFECTING BEAUTY BALM SUNSCREEN BROAD SPECTRUM SPF 20 FAIR 01

Active ingredients

Octinoxate 6%
Titanium dioxide 2%

Purpose

Sunscreen

Uses

- Helps prevent sunburn.
- If used as directed with other sun protection measures (see Directions), decreases the risk of skin cancer and early aging caused by the sun.

Warnings

For external use only.

Do not use

- on damaged or broken skin

When using this product

- keep out of eyes. Rinse with water to remove.

Stop use and ask a doctor

- if rash occurs

Keep out of reach of children.

If swallowed, get medical help or contact a Poison Control Center right away.

Directions

- Apply liberally 15 min before sun exposure
- Reapply at least every 2 hrs
- Use a water resistant sunscreen if swimming or sweating
- Sun Protection Measures. Spending time in the sun increases your risk of skin cancer and early skin aging. To decrease this risk, regularly use a sunscreen with a Broad Spectrum SPF value of 15 or higher and other sun protection measures including:
- Limit time in the sun, especially from 10am-2pm
- Wear long-sleeved shirts, pants, hats and sunglasses
- Children under 6 months of age: Ask a doctor

Other information

- Protect the product in this container from excessive heat and direct sun.
- Store container in upright position.

Inactive ingredients

water, diethylhexyl carbonate, ethylhexyl stearate, diisostearoyl polyglyceryl-3 dimer dilinoleate, cyclopentasiloxane, microcrystalline wax, hydrogenated castor oil, cetyl peg/ppg-10/1 dimethicone, polyglyceryl-4 isostearate, silica, hexyl laurate, sodium chloride, phenoxyethanol, cetyl dimethicone, potassium sorbate, sodium dehydroacetate, dimethicone, corn oil, nylon-12 fluorescent brightener 230 salt, propylene glycol dicaprylate/dicaprate, caprylic/capric triglyceride, tetrasodium EDTA, fragrance, hydrogenated vegetable oil, ascorbyl palmitate, tea (camellia sinensis) leaf extract, tocopheryl acetate, aminomethyl propanol, alpha-isomethyl ionone, polyvinylalcohol crosspolymer, spanish lavender (lavandula stoechas) extract, BHT, benzyl benzoate, hydroxycitronellal, dog rose (rosa canina) fruit extract, mica, titanium dioxide, iron oxides.